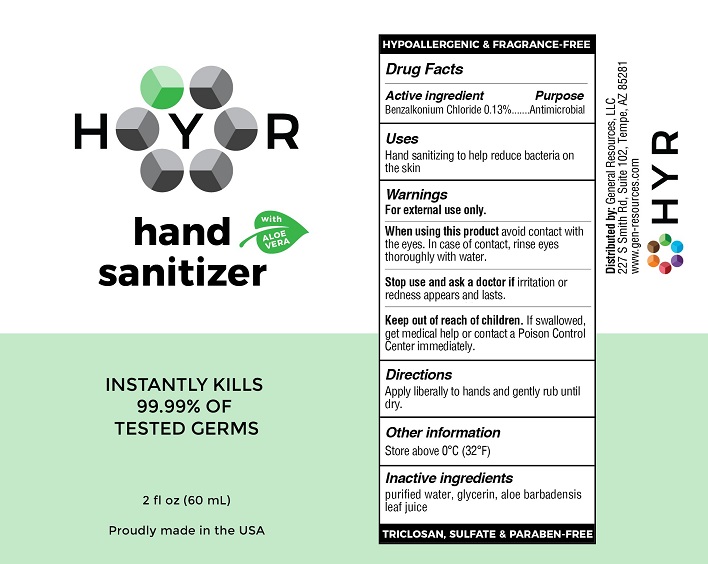 DRUG LABEL: HYR Hand Sanitizer with Aloe Vera
NDC: 70481-301 | Form: SOLUTION
Manufacturer: General Resources LLC
Category: otc | Type: HUMAN OTC DRUG LABEL
Date: 20201026

ACTIVE INGREDIENTS: BENZALKONIUM CHLORIDE 0.13 g/100 mL
INACTIVE INGREDIENTS: WATER; ALOE VERA LEAF; GLYCERIN

HYR Hand Sanitizer with Aloe and Glycerin

Drug Facts

Active ingredient

Benzalkonium Chloride 0.13%

Purpose

Antimicrobial

Uses

Hand sanitizing to help reduce bacteria on the skin

Warnings

For external use only.

When using this product avoid contact with the eyes. In case of contact, rinse eyes thoroughly with water.

Stop use and ask a doctor if irritation or redness appears and lasts

Keep out of reach of children. If swallowed, get medical help or contact a Poison Control Center immediately.

Directions

Apply liberally to hands and gently rub until dry.

Other information

Store above 0°C (32°F)

Inactive ingredients

purified water, glycerin, aloe barbadensis leaf juice

Distributed by: General Resources, LLC

227 S. Smith Rd, Suite 102, Tempe, AZ 85281

www.gen-resources.com

PACKAGE LABEL

HYR

hand sanitizer WITH ALOE VERA

INSTANTLY KILLS 99.99% OF TESTED GERMS

2 fl oz (60 mL)

Proudly made in the USA